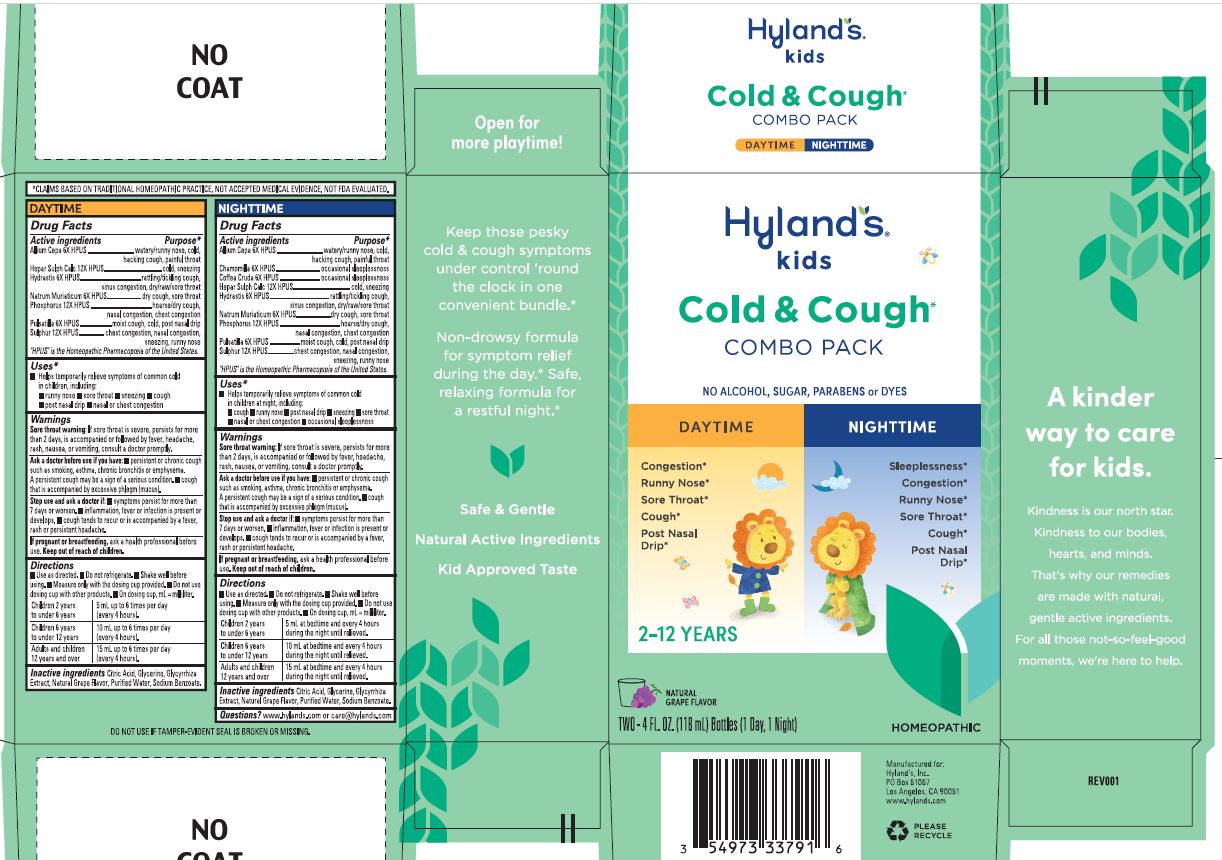 DRUG LABEL: 4 Kids Cold and Cough Day and Night Grape Flavor
NDC: 54973-3379 | Form: KIT | Route: ORAL
Manufacturer: Hyland's Inc.
Category: homeopathic | Type: HUMAN OTC DRUG LABEL
Date: 20251219

ACTIVE INGREDIENTS: ONION 6 [hp_X]/1 mL; GOLDENSEAL 6 [hp_X]/1 mL; CALCIUM SULFIDE 12 [hp_X]/1 mL; SODIUM CHLORIDE 6 [hp_X]/1 mL; PHOSPHORUS 12 [hp_X]/1 mL; ANEMONE PULSATILLA 6 [hp_X]/1 mL; SULFUR 12 [hp_X]/1 mL; ANEMONE PULSATILLA 6 [hp_X]/1 mL; SULFUR 12 [hp_X]/1 mL; CALCIUM SULFIDE 12 [hp_X]/1 mL; GOLDENSEAL 6 [hp_X]/1 mL; SODIUM CHLORIDE 6 [hp_X]/1 mL; MATRICARIA CHAMOMILLA 6 [hp_X]/1 mL; ARABICA COFFEE BEAN 6 [hp_X]/1 mL; ONION 6 [hp_X]/1 mL; PHOSPHORUS 12 [hp_X]/1 mL
INACTIVE INGREDIENTS: CITRIC ACID MONOHYDRATE; GLYCERIN; GLYCYRRHIZA GLABRA; WATER; SODIUM BENZOATE; CITRIC ACID MONOHYDRATE; GLYCERIN; WATER; GLYCYRRHIZA GLABRA; SODIUM BENZOATE

Hyland's Kids Cold 'n Cough Day & Night Combo Pack Grape Flavor

PURPOSE

Relieves congestion, runny nose, sore throat, sneezing, cough, post nasal drip and occasional sleeplessness

DAYTIME

Drug Facts

Active ingredients | Purpose
Allium Cepa 6X HPUS | watery/runny nose, cold, hacking cough, painful throat
Hepar Sulph Calc 12X HPUS | cold, sneezing
Hydrastis 6X HPUS | rattling/tickling cough, sinus congestion, dry/raw/sore throat
Natrum Muriaticum 6X HPUS | dry cough, sore throat
Phosphorus 12X HPUS | hoarse/dry cough, nasal congestion, chest congestion
Pulsatilla 6X HPUS | moist cough, cold, post nasal drip
Sulphur 12X HPUS | chest congestion, nasal congestion, sneezing, runny nose

"HPUS" indicates that the active ingredients are in the official Homeopathic Pharmacopoeia of the United States.

Uses

■ Temporarily relieves symptoms of common cold
in children, including:
■ runny nose ■ sore throat ■ sneezing
■ cough ■ post nasal drip
■ nasal or chest congestion

Warnings

Sore throat warning: If sore throat is severe, persists for more than 2 days, is accompanied or followed by fever, headache,
rash, nausea, or vomiting, consult a doctor promptly.

Ask a doctor before use if you have: ■ persistent or chronic cough such as smoking, asthma, chronic bronchitis or emphysema. A persistent cough may be a sign of a serious condition. ■ cough that is accompanied by excessive phlegm (mucus).

Stop use and ask a doctor if: ■ symptoms persist for more than 7 days or worsen. ■ inflammation, fever or infection is present or develops. ■ cough tends to recur or is accompanied by a fever, rash or persistent headache.

PREGNANCY OR BREAST FEEDING

If pregnant or breastfeeding, ask a health professional before use.

Keep out of reach of children.

Directions

■ Use as directed. ■ Do not refrigerate. ■ Shake well before
using. ■ Measure only with the dosing cup provided. ■ Do not use
dosing cup with other products. ■ On dosing cup, mL = milliliter.

Children 2 years to under 6 years | 5 mL up to 6 times per day (every 4 hours).
Children 6 years to under 12 years | 10 mL up to 6 times per day (every 4 hours).
Adults and children 12 years and over | 15 mL up to 6 times per day (every 4 hours).

Inactive ingredients

Citric Acid, Glycerine, Glycyrrhiza Extract, Natural Grape Flavor, Purified Water, Sodium Benzoate.

NIGHTTIME

Drug Facts

Active ingredients | Purpose
Allium Cepa 6X HPUS | watery/runny nose, cold, hacking cough, painful throat
Chamomilla 6X HPUS | occasional sleeplessness
Coffea Cruda 6X HPUS | occasional sleeplessness
Hepar Sulph Calc 12X HPUS | cold, sneezing
Hydrastis 6X HPUS | rattling/tickling cough, sinus congestion, dry/raw/sore throat
Natrum Muriaticum 6X HPUS | dry cough, sore throat
Phosphorus 12X HPUS | hoarse/dry cough, nasal congestion, chest congestion
Pulsatilla 6X HPUS | moist cough, cold, post nasal drip
Sulphur 12X HPUS | chest congestion, nasal congestion, sneezing, runny nose

HPUS" indicates that the active ingredients are in the official Homeopathic Pharmacopoeia of the United States.

Uses

■ Temporarily relieves symptoms of common cold
in children at night, including:
■ cough ■ runny nose ■ post nasal drip
■ sneezing ■ nasal or chest congestion
■ sore throat ■ occasional sleeplessness

Warnings

Sore throat warning: If sore throat is severe, persists for more than 2 days, is accompanied or followed by fever, headache,
rash, nausea, or vomiting, consult a doctor promptly.

Ask a doctor before use if you have: ■ persistent or chronic cough such as smoking, asthma, chronic bronchitis or emphysema. A persistent cough may be a sign of a serious condition. ■ cough that is accompanied by excessive phlegm (mucus).

Stop use and ask a doctor if: ■ symptoms persist for more than 7 days or worsen. ■ inflammation, fever or infection is present or develops. ■ cough tends to recur or is accompanied by a fever, rash or persistent headache.

PREGNANCY OR BREAST FEEDING

If pregnant or breastfeeding, ask a health professional before use.

Keep out of reach of children.

Directions

■ Use as directed. ■ Do not refrigerate. ■ Shake well before
using. ■ Measure only with the dosing cup provided. ■ Do not use
dosing cup with other products. ■ On dosing cup, mL = milliliter.

Children 2 years to under 6 years | 5 mL at bedtime and every 4 hours during the night until relieved.
Children 6 years to under 12 years | 10 mL at bedtime and every 4 hours during the night until relieved.
Adults and children 12 years and over | 15 mL at bedtime and every 4 hours during the night until relieved.

Inactive ingredients

Citric Acid, Glycerine, Glycyrrhiza Extract, Natural Grape Flavor, Purified Water, Sodium Benzoate.

Questions?

(800) 624-9659

*CLAIMS BASED ON TRADITIONAL HOMEOPATHIC PRACTICE, NOT ACCEPTED MEDICAL EVIDENCE. NOT FDA EVALUATED.

DO NOT USE IF TAMPER-EVIDENT SEAL IS BROKEN OR MISSING.

Indications and Usage

update:

Uses

- Temporarily relieves symptoms of common cold in children, including:
- runny nose 
- sore throat
- sneezing
- cough 
- post nasal drip
- nasal or chest congestion

Dosage and Administration

Directions

- 5 mL up to 6 times per day

(every 4 hours)

- 10 mL up to 6 times per day

(every 4 hours)

- 15 mL up to 6 times per day

(every 4 hours)

PACKAGE LABEL - KIT CARTON

Hyland's

•KIDS•

Cold & Cough

COMBO PACK

NO ALCOHOL, SUGAR,

PARABENS or DYES

DAYTIME

Congestion

Runny Nose

Sore Throat

Cough

Post Nasal

Drip

NIGHTTIME

Sleeplessness

Congestion

Runny Nose

Sore Throat

Cough

Post Nasal

Drip

2-12 YEARS

NATURAL

GRAPE FLAVOR

TWO - 4 FL. OZ. (118 mL) Bottles (1 Day, 1 Night) | TOTAL 8 FL. OZ. (236 ML)

HOMEOPATHIC